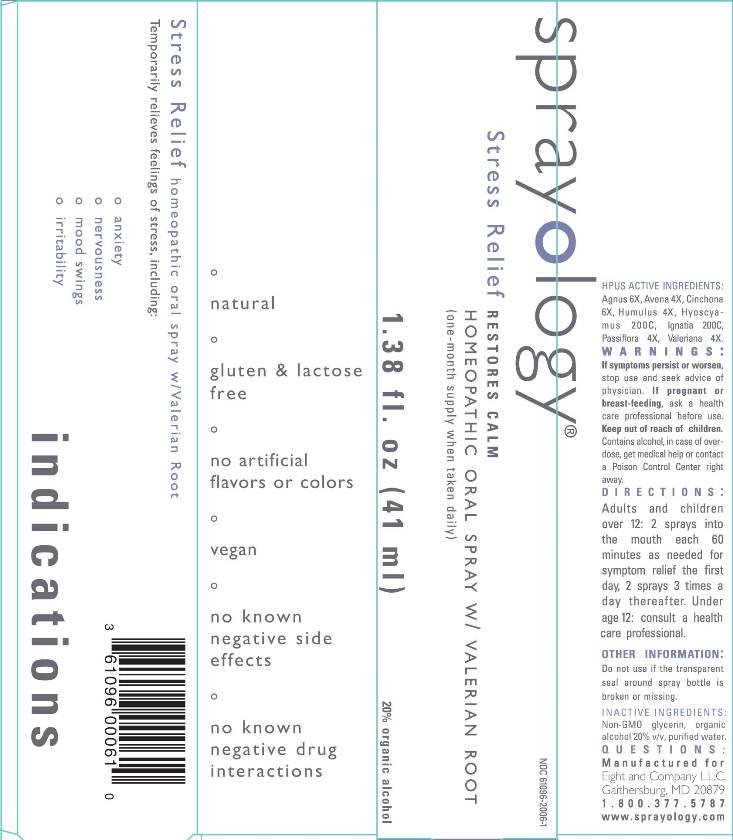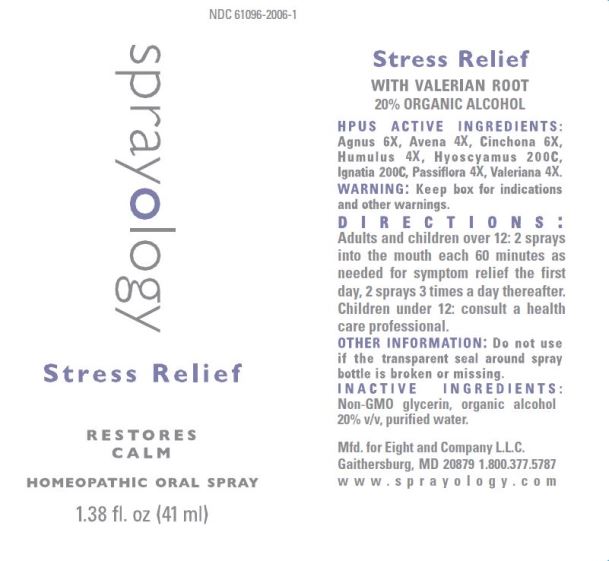 DRUG LABEL: Sprayology Stress Relief
NDC: 61096-2006 | Form: LIQUID
Manufacturer: Eight and Company L.L.C
Category: homeopathic | Type: HUMAN OTC DRUG LABEL
Date: 20251217

ACTIVE INGREDIENTS: CHASTE TREE 6 [hp_X]/41 mL; AVENA SATIVA FLOWERING TOP 4 [hp_X]/41 mL; CINCHONA OFFICINALIS BARK 6 [hp_X]/41 mL; HOPS 4 [hp_X]/41 mL; HYOSCYAMUS NIGER 200 [hp_C]/41 mL; STRYCHNOS IGNATII SEED 200 [hp_C]/41 mL; PASSIFLORA INCARNATA FLOWERING TOP 4 [hp_X]/41 mL; VALERIAN 4 [hp_X]/41 mL
INACTIVE INGREDIENTS: GLYCERIN; ALCOHOL; WATER

Sprayology Stress Relief

ACTIVE INGREDIENTS:

Agnus 6X, Avena 4X, Cinchona 6X, Humulus 4X, Hyoscyamus 200C, Ignatia 200C, Passiflora 4X, Valeriana 4X

PURPOSE:

Temporarily relieves feelings of stress, including:

- anxiety
- nervousness
- mood swings
- irritability

WARNINGS:

If symptoms persist or worsen, stop use and seek advice of physician. If pregnant or breast-feeding, ask a health care professional before use. Keep out of reach of children. Contains alcohol, in case of overdose, get medical help or contact a Poison Control Center right away.

Keep out of reach of children. Contains alcohol, in case of overdose, get medical help or contact a Poison Control Center right away.

DIRECTIONS:

Adults and children over 12: 2 sprays into the mouth each 60 minutes as needed for symptom relief the first day, 2 sprays 3 times a day thereafter.

Under age 12: consult a health care professional.

OTHER INFORMATION:

Do not use if the transparent seal around spray bottle is broken or missing.

INDICATIONS:

Temporarily relieves feelings of stress, including:

° anxiety

° nervousness

° mood swings

° irritability

° natural

° gluten & lactose free

° no artificial flavors or colors

° no known negative side effects

° no known negative drug interactions

INACTIVE INGREDIENTS:

Non-GMO glycerin, v/v, organic alcohol 20% v/v and purified water.

QUESTIONS:

Mfd. for Eight and Company L.L.C.

Gaithersburg, MD 20879 1.800.377.5787

www.sprayology.com

PACKAGE LABEL DISPLAY:

NDC 61096-2006-1

sprayology

Stress Relief

RESTORES CALM

HOMEOPATHIC ORAL SPRAY

1.38 fl.oz (41 ml)